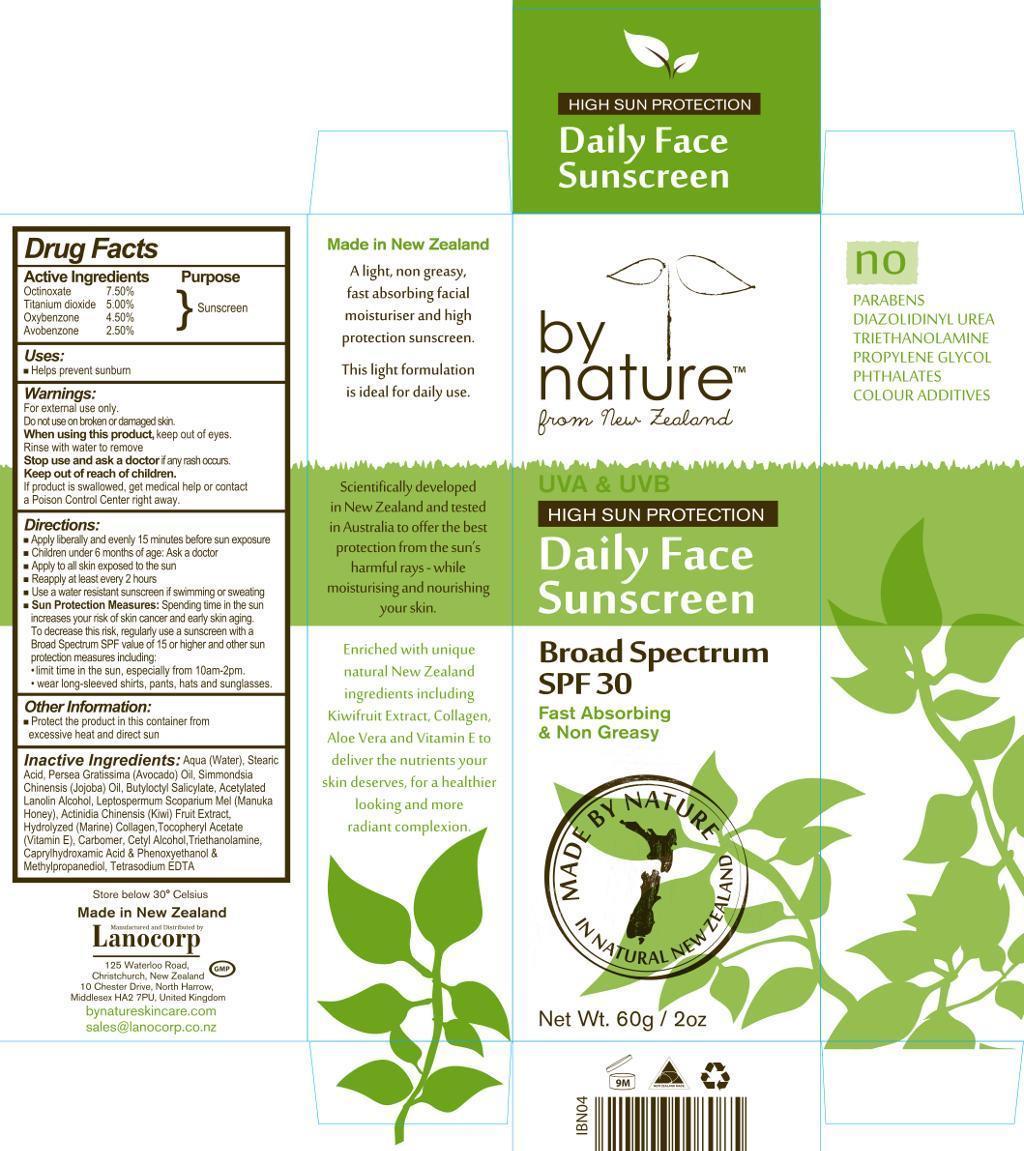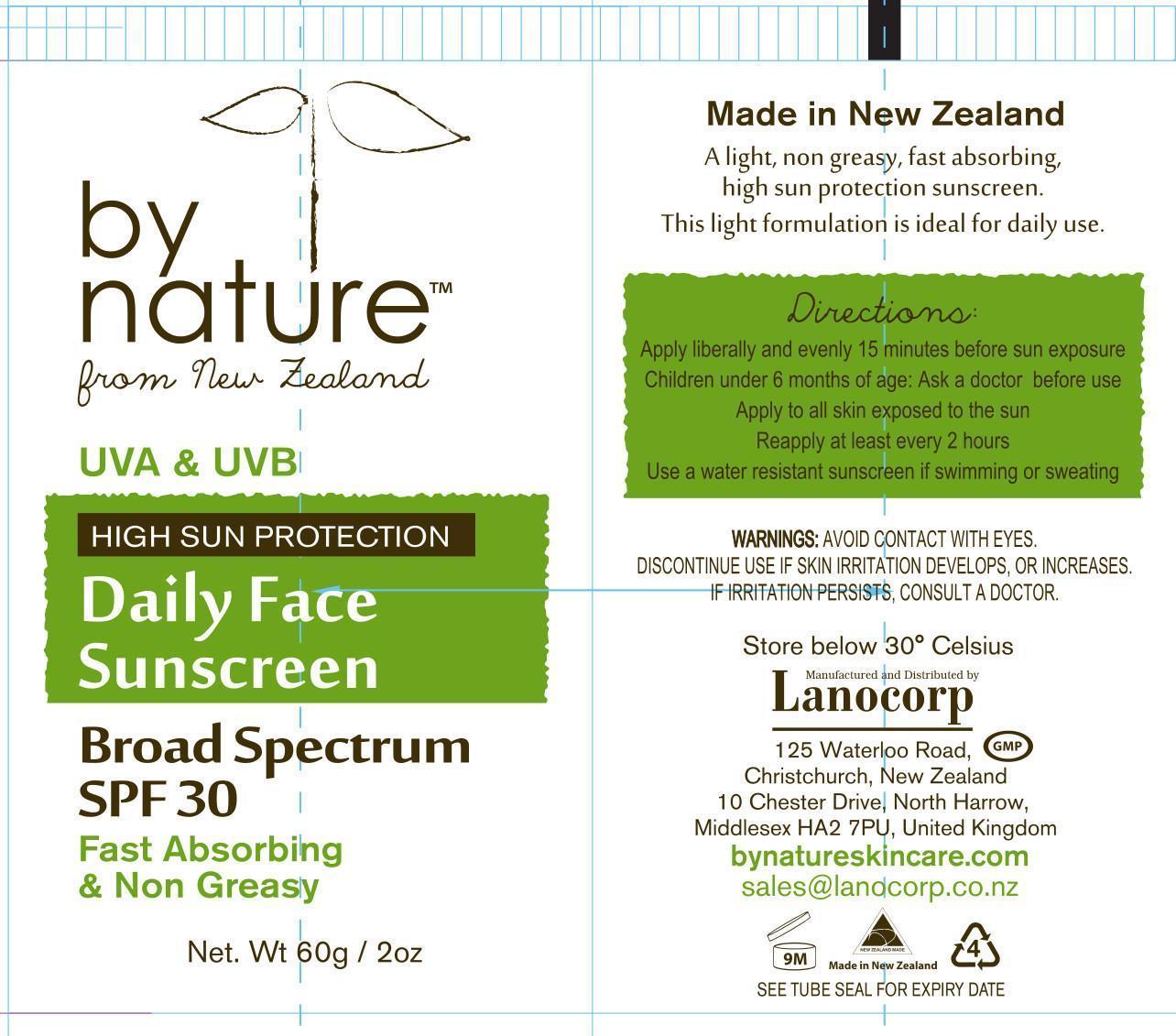 DRUG LABEL: By Nature Daily Face Sunscreen 
NDC: 43617-3417 | Form: CREAM
Manufacturer: Lanocorp Pacific Ltd
Category: otc | Type: HUMAN OTC DRUG LABEL
Date: 20140122

ACTIVE INGREDIENTS: OCTINOXATE 75 g/1 g; TITANIUM DIOXIDE 50 g/1 g; OXYBENZONE 45 g/1 g; AVOBENZONE 25 g/1 g
INACTIVE INGREDIENTS: WATER; STEARIC ACID; AVOCADO OIL; JOJOBA OIL; BUTYLOCTYL SALICYLATE; ACETYLATED LANOLIN ALCOHOLS; HONEY; KIWI FRUIT; HYDROLYSED MARINE COLLAGEN (ENZYMATIC; 2000 MW); .ALPHA.-TOCOPHEROL ACETATE ; CARBOMER HOMOPOLYMER TYPE A (ALLYL PENTAERYTHRITOL CROSSLINKED) ; CETYL ALCOHOL; TROLAMINE; CAPRYLHYDROXAMIC ACID; PHENOXYETHANOL; METHYLPROPANEDIOL; EDETATE SODIUM

DRUG FACTS

ACTIVE INGREDIENTS

Octinoxate 7,50%
Titanium dioxide 5,00%
Oxybenzone 4,50%
Avobenzone 2,5%

PURPOSE

Sunscreen

USES

Helps prevent sunburn

WARNINGS

For external use only.
Do not use on broken or damaged skin.

When using this product, keep out of eyes.
Rinse with water to remove.

Stop use and ask a doctor if any rush occurs.

Keep out of reach of children.
If product is swalowed, get medical help or contact a Poison Control Center right away.

DIRECTIONS

Apply liberally and evenly 15 minutes before sun exposure
Children under 6 months of age: Ask a doctor
Apply to all skin exposed to the sun
Reapply at least every 2 hours
Use a water resistant sunscreen if swimming or sweating
Sun protection measures: Spending time in the sun increases your risk of skin cancer and early skin aging.
To decrease this risk, regularly use a sunscreen with a Broad Spectrum SPF value of 15 or higher and other sun protection measures including:
- limit time in the sun, especially from 10am-2pm.
- wear long-sleeved shirts, pants, hats and sunglasses.

OTHER INFORMATION

Protect the product in this container from excessive heat and direct sun

INACTIVE INGREDIENTS

Aqua (water)
Stearic Acid
Persea Gratissima (Avocado) Oil
Simmondsia Chinensis (Jojoba) Oil
Butyloctyl salicylate
Acetylated Lanolin Alcohol
Leptospermum Scoparium Mel
Actinidia Chinensis (Kiwi) Fruit Extract
Hydrolyzed (Marine) Collagen
Tocopheryl Acetate (Vitamin E)
Carbomer
Cetyl Alcohol
Triethanolamine
Caprylhydroxamic Acid
Phenoxiethanol
Methylpropanediol
Tetrasodium EDTA